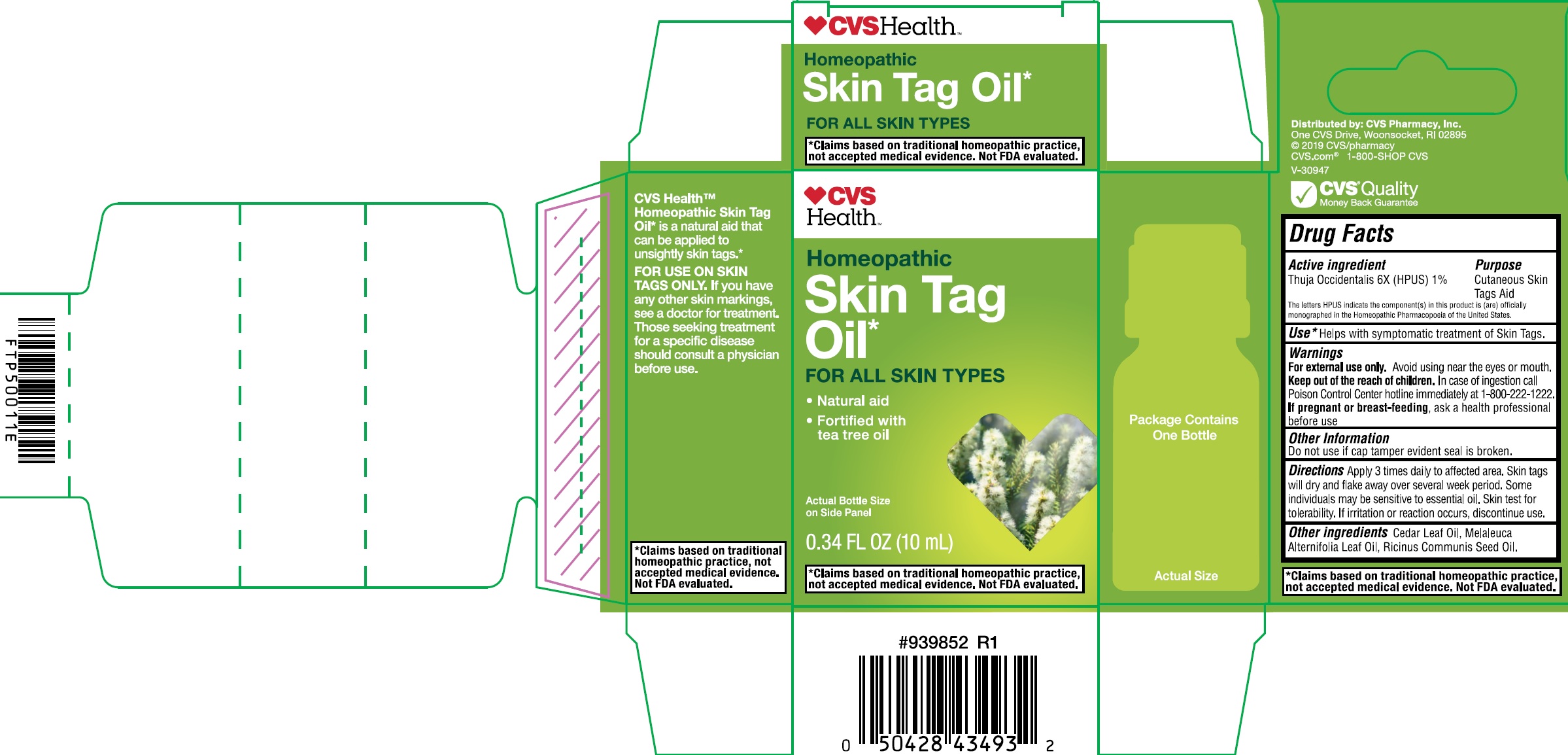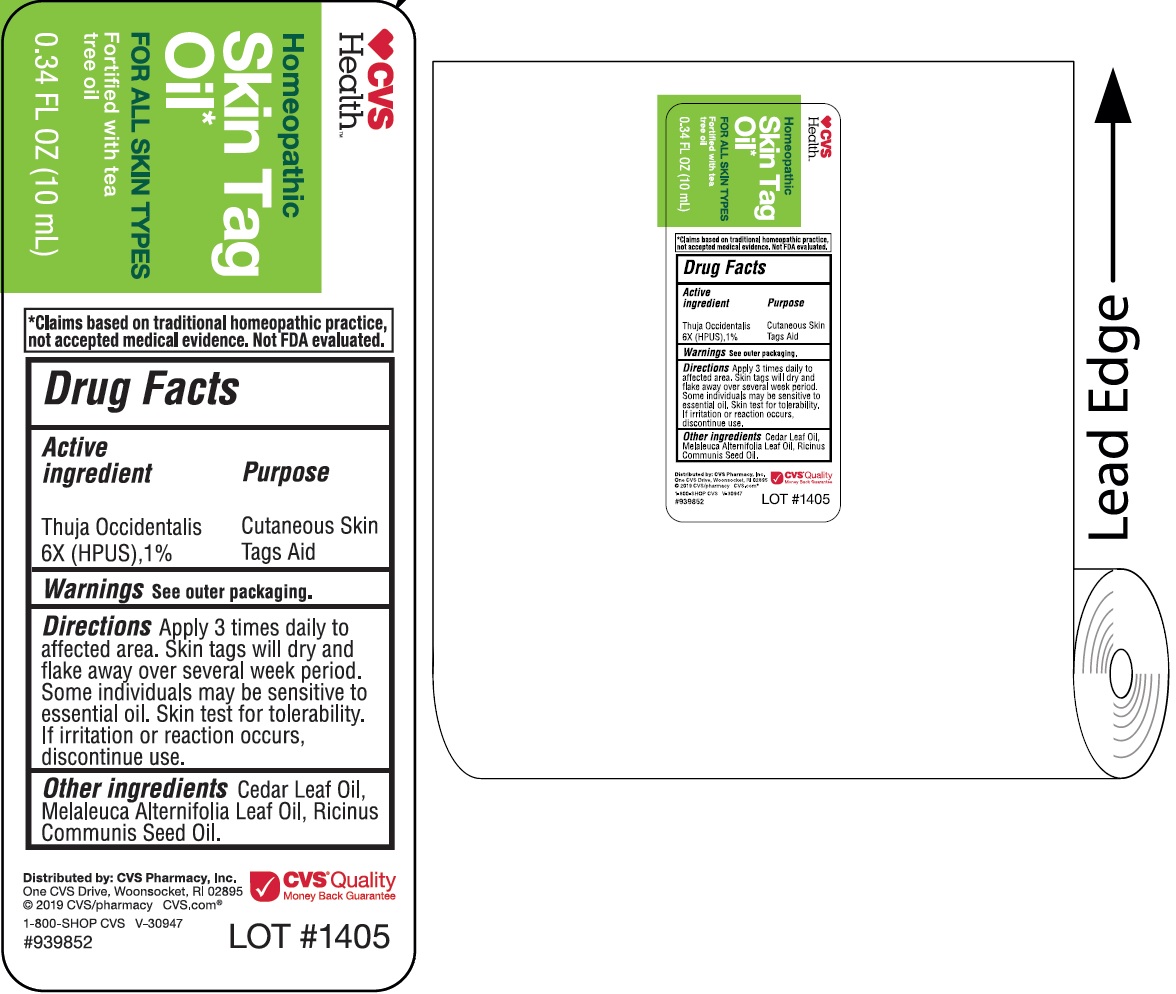 DRUG LABEL: CVS Skin Tag
NDC: 69842-965 | Form: OIL
Manufacturer: CVS Pharmacy
Category: homeopathic | Type: HUMAN OTC DRUG LABEL
Date: 20200108

ACTIVE INGREDIENTS: THUJA OCCIDENTALIS LEAFY TWIG 6 [hp_X]/10 mL
INACTIVE INGREDIENTS: CEDAR LEAF OIL; TEA TREE OIL; CASTOR OIL

CVS Skin Tag Oil

Active ingredient

Thuja Occidentails 6X (HPUS) 1%

Purpose

Cutaneous Skin Tags Aid

The letters HPUS indicate the component(s) in this product is (are) officially monographed in the Homeopathic Pharmacopoeia of the United States.

Use

*Helps with symptomatic treatment of Skin Tags.

Warnings

For external use only. Avoid using near the eyes or mouth.

Keep out of the reach of children.

In case of ingestion call Poison Control Center hotline immediately at 1-800-222-1222.

If pregnant or breast-feeding,

ask a health professional before use

Other Information

Do not use if cap tamper evident seal is broken.

Directions

Apply 3 times daily to affected area. Skin tags will dry and flake away over several week period. Some individuals may be sensitive to essential oil. Skin test for tolerability. If irritation or reaction occurs, disconrinue use.

Other ingredients

Cedar Leaf Oil, Melaleuca Alternifolia Leaf Oil, Ricinus Communis Seed Oil.